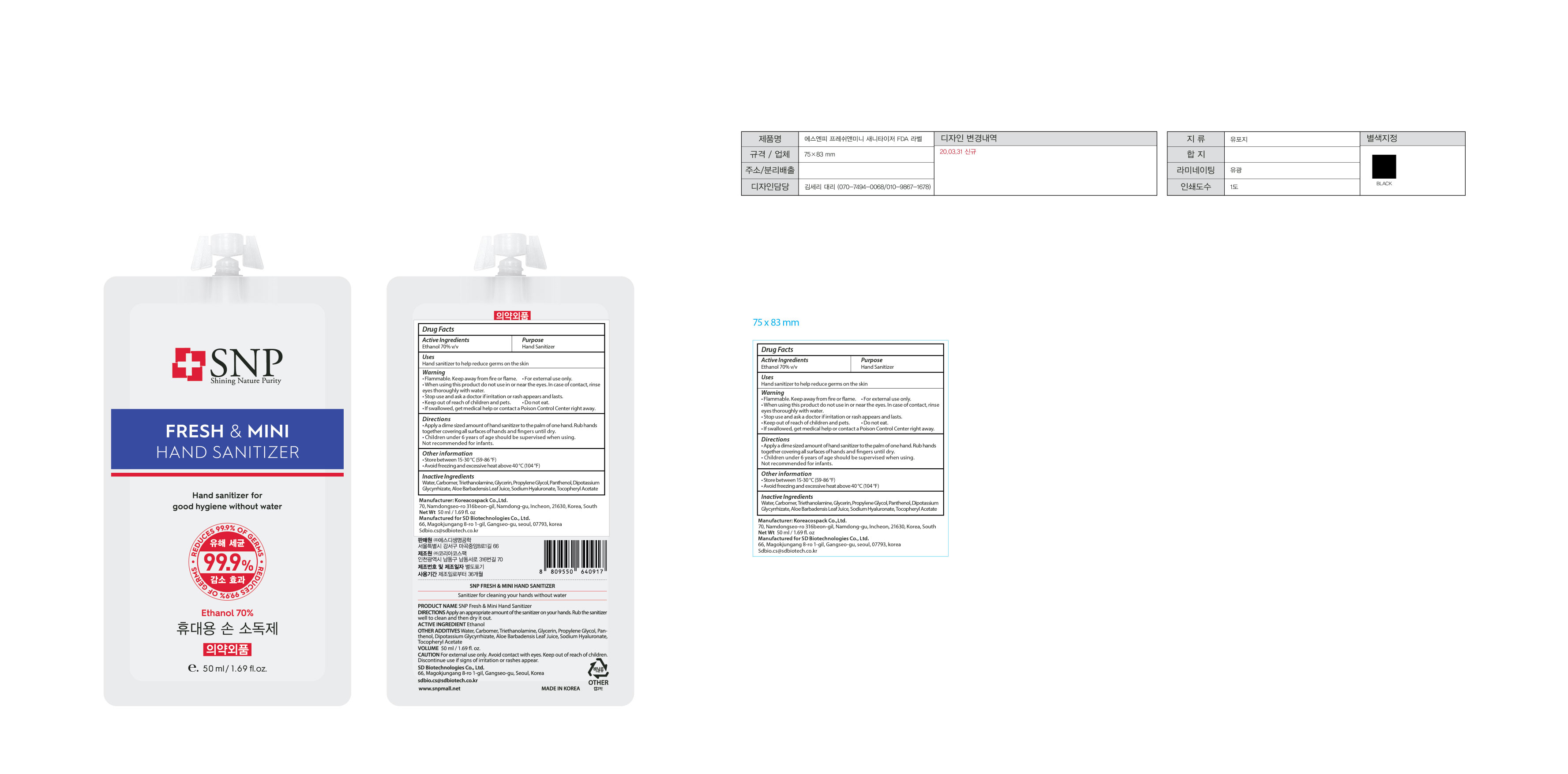 DRUG LABEL: FRESH AND MINI HAND SANITIZER
NDC: 74064-7050 | Form: GEL
Manufacturer: KOREA COSPACK CO.,LTD.
Category: otc | Type: HUMAN OTC DRUG LABEL
Date: 20200411

ACTIVE INGREDIENTS: ALCOHOL 35 mL/50 mL
INACTIVE INGREDIENTS: .ALPHA.-TOCOPHEROL ACETATE; HYALURONATE SODIUM; TROLAMINE; GLYCERIN; CARBOMER HOMOPOLYMER, UNSPECIFIED TYPE; WATER; PROPYLENE GLYCOL; PANTHENOL; GLYCYRRHIZINATE DIPOTASSIUM; ALOE VERA LEAF

[SD Biotechnologies Co., Ltd.] 50 ml : 74064-7050